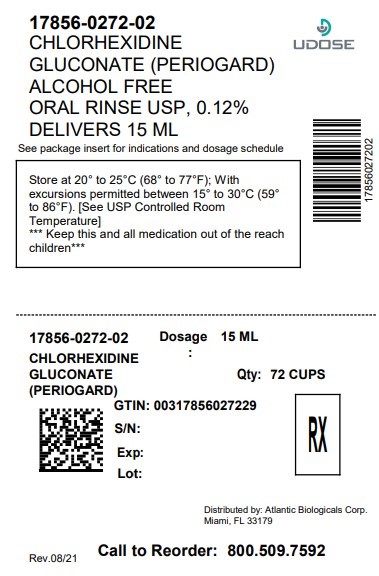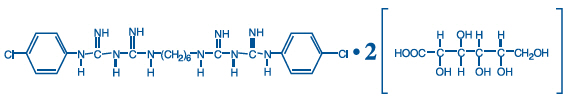 DRUG LABEL: Periogard Alcohol Free
NDC: 17856-0272 | Form: RINSE
Manufacturer: ATLANTIC BIOLOGICALS CORP.
Category: prescription | Type: HUMAN PRESCRIPTION DRUG LABEL
Date: 20260213

ACTIVE INGREDIENTS: CHLORHEXIDINE GLUCONATE 1.2 mg/1 mL
INACTIVE INGREDIENTS: WATER; PROPYLENE GLYCOL; GLYCERIN; SORBITOL; PEG-40 CASTOR OIL; CETYLPYRIDINIUM CHLORIDE; FD&C BLUE NO. 1

PerioGard®
(Chlorhexidine Gluconate
Oral Rinse USP, 0.12%)

NDC

17856-0272-01

17856-0272-02

17856-0272-03

DESCRIPTION

PerioGard® (Chlorhexidine Gluconate Oral rinse USP, 0.12%) is an oral rinse containing 0.12% chlorhexidine gluconate (1,1'-hexamethylene bis [5-(p-chlorophenyl) biguanide] di-D-gluconate) in a base containing water, propylene glycol, glycerin, sorbitol, polyoxyl 40 hydrogenated castor oil, flavor, cetylpyridinium chloride, and FD&C blue no. 1. PerioGard® product is a near neutral solution (pH range 5-7). Chlorhexidine gluconate is a salt of chlorhexidine and gluconic acid. Its chemical structure is:

CLINICAL PHARMACOLOGY

PerioGard® (Chlorhexidine Gluconate Oral Rinse USP, 0.12%) provides antimicrobial activity during oral rinsing. The clinical significance of chlorhexidine gluconate oral rinse's antimicrobial activities is not clear. Microbiological sampling of plaque has shown a general reduction of counts of certain assayed bacteria, both aerobic and anaerobic, ranging from 54-97% through six months' use.

Use of chlorhexidine gluconate oral rinse USP, 0.12% in a six-month clinical study did not result in any significant changes in bacterial resistance, overgrowth of potentially opportunistic organisms or other adverse changes in the oral microbial ecosystem. Three months after chlorhexidine gluconate oral rinse USP, 0.12% use was discontinued, the number of bacteria in plaque had returned to baseline levels and resistance of plaque bacteria to chlorhexidine gluconate was equal to that at baseline.

PHARMACOKINETICS

Pharmacokinetic studies with a chlorhexidine gluconate oral rinse USP, 0.12% indicate approximately 30% of the active ingredient is retained in the oral cavity following rinsing. This retained drug is slowly released into the oral fluids.

Studies conducted on human subjects and animals demonstrate chlorhexidine gluconate is poorly absorbed from the gastrointestinal tract. The mean plasma level of chlorhexidine gluconate reached a peak of 0.206 µg/g in humans 30 minutes after they ingested a 300-mg dose of the drug. Detectable levels of chlorhexidine gluconate were not present in the plasma of these subjects 12 hours after the compound was administered. Excretion of chlorhexidine gluconate occurred primarily through the feces (~90%). Less than 1% of the chlorhexidine gluconate ingested by these subjects was excreted in the urine.

INDICATIONS AND USAGE

PerioGard® (Chlorhexidine Gluconate Oral Rinse USP, 0.12%) is indicated for use between dental visits as part of a professional program for the treatment of gingivitis as characterized by redness and swelling of the gingivae, including gingival bleeding upon probing. PerioGard® has not been tested among patients with acute necrotizing ulcerative gingivitis (ANUG). For patients having coexisting gingivitis and periodontitis, see PRECAUTIONS.

CONTRAINDICATIONS

PerioGard® should not be used by persons who are known to be hypersensitive to chlorhexidine gluconate or other formula ingredients.

WARNINGS

The effect of PerioGard® on periodontitis has not been determined. An increase in supragingival calculus was noted in clinical testing with users of chlorhexidine gluconate oral rinse USP, 0.12% compared with control users. It is not known if chlorhexidine gluconate use results in an increase of subgingival calculus. Calculus deposits should be removed by a dental prophylaxis at intervals not greater than six months. Anaphylaxis, as well as serious allergic reactions, have been reported during postmarketing use with dental products containing chlorhexidine.

SEE CONTRAINDICATIONS.

PRECAUTIONS

General

1. For patients having coexisting gingivitis and periodontitis, the presence or absence of gingival inflammation following treatment with PerioGard® (Chlorhexidine Gluconate Oral Rinse USP, 0.12%) should not be used as a major indicator of underlying periodontitis.

2. PerioGard® can cause staining of oral surfaces, such as tooth surfaces, restorations, and the dorsum of the tongue. Not all patients will experience a visually significant increase in tooth staining. In clinical testing, 56% of the chlorhexidine gluconate oral rinse USP, 0.12% users exhibited a measurable increase in facial anterior stain, compared to 35% of control users after six months; 15% of the chlorhexidine gluconate oral rinse USP, 0.12% users developed what was judged to be heavy stain, compared to 1% of control users after six months. Stain will be more pronounced in patients who have heavier accumulations of unremoved plaque. Stain resulting from the use of PerioGard® does not adversely affect health of the gingivae or other oral tissues. Stain can be removed from most tooth surfaces by conventional professional prophylactic techniques. Additional time may be required to complete the prophylaxis. Discretion should be used when prescribing to patients with anterior facial restorations with rough surfaces or margins. If natural stain cannot be removed from these surfaces by a dental prophylaxis, patients should be excluded from PerioGard® treatment if permanent discoloration is unacceptable. Stain in these areas may be difficult to remove by dental prophylaxis and on rare occasions may necessitate replacement of these restorations.

3. Some patients may experience an alteration in taste perception while undergoing treatment with a chlorhexidine gluconate oral rinse USP, 0.12%. Rare instances of permanent taste alteration following chlorhexidine gluconate oral rinse USP, 0.12% use have been reported via postmarketing product surveillance.

Pregnancy

Teratogenic Effects

Pregnancy Category B

Reproduction studies have been performed in rats and rabbits at chlorhexidine gluconate doses up to 300 mg/kg/day and 40 mg/kg/day, respectively, and have not revealed evidence of harm to fetus. However, adequate and well-controlled studies in pregnant women have not been done. Because animal reproduction studies are not always predictive of human response, this drug should be used during pregnancy only if clearly needed.

Nursing Mothers

It is not known whether this drug is excreted in human milk. Because many drugs are excreted in human milk, caution should be exercised when PerioGard® (Chlorhexidine Gluconate Oral Rinse USP, 0.12%) is administered to nursing women. In parturition and lactation studies with rats, no evidence of impaired parturition or of toxic effects to suckling pups was observed when chlorhexidine gluconate was administered to dams at doses that were over 100 times greater than that which would result from a person's ingesting 30 mL (2 doses) of PerioGard® per day.

Pediatric Use

Clinical effectiveness and safety of PerioGard® have not been established in children under the age of 18.

Carcinogenesis, Mutagenesis, Impairment of Fertility

In a drinking water study in rats, carcinogenic effects were not observed at doses up to 38 mg/kg/day. Mutagenic effects were not observed in two mammalian in vivomutagenesis studies with chlorhexidine gluconate. The highest doses of chlorhexidine used in a mouse dominant-lethal assay and a hamster cytogenetics test were 1000 mg/kg/day and 250 mg/kg/day, respectively. No evidence of impaired fertility was observed in rats at doses up to 100 mg/kg/day.

ADVERSE REACTIONS

The most common side effects associated with chlorhexidine gluconate oral rinse USP, 0.12% are: (1) an increase in staining of teeth and other oral surfaces, (2) an increase in calculus formation, and (3) an alteration in taste perception; see WARNINGSand PRECAUTIONS. Oral irritation and local allergy-type symptoms have been spontaneously reported as side effects associated with use of chlorhexidine gluconate rinse. The following oral mucosal side effects were reported during placebo-controlled adult clinical trials: aphthous ulcer, grossly obvious gingivitis, trauma, ulceration, erythema, desquamation, coated tongue, keratinization, geographic tongue, mucocele, and short frenum. Each occurred at a frequency of less than 1.0%.

Among postmarketing reports, the most frequently reported oral mucosal symptoms associated with chlorhexidine gluconate oral rinse USP, 0.12% are stomatitis, gingivitis, glossitis, ulcer, dry mouth, hypesthesia, glossal edema, and paresthesia.

Minor irritation and superficial desquamation of the oral mucosa have been noted in patients using chlorhexidine gluconate oral rinse.

There have been cases of parotid gland swelling and inflammation of the salivary glands (sialadenitis) reported in patients using chlorhexidine gluconate oral rinse.

OVERDOSAGE

Ingestion of 1 or 2 ounces of PerioGard® (Chlorhexidine Gluconate Oral Rinse USP, 0.12%) by a small child (~10 kg body weight) might result in gastric distress, including nausea. Medical attention should be sought if more than 4 ounces of PerioGard® Oral Rinse is ingested by a small child.

DOSAGE AND ADMINISTRATION

PerioGard® (Chlorhexidine Gluconate Oral Rinse USP, 0.12%) therapy should be initiated directly following a dental prophylaxis. Patients using PerioGard® should be reevaluated and given a thorough prophylaxis at intervals no longer than six months. Recommended use is twice daily oral rinsing for 30 seconds, morning and evening after toothbrushing. Usual dosage is 1/2 fl. oz. ("15 mL" line in dosage cap) of undiluted PerioGard®. Patients should be instructed not to rinse with water or other mouthwashes, brush teeth, or eat immediately after using PerioGard®. PerioGard® is not intended for ingestion and should be expectorated after rinsing.

HOW SUPPLIED

PerioGard® is supplied as a blue liquid in 3 different UD presentations

5 ML UD CUP............................... NDC 17856-0272-03

10 ML UD CUP............................. NDC 17856-0272-01

15 ML UD CUP............................. NDC 17856-0272-02

STORAGE AND HANDLING

Store at 20° to 25°C (68° to 77°F) excursions permitted between 15° to 30°C (59° to 86°F) [see USP Controlled Room Temperature].

Rx Only. Keep out of reach of children.

DISTRIBUTED BY:

ATLANTIC BIOLOGICALS CORP.

MIAMI, FL 33179

PRINCIPAL DISPLAY PANEL

PerioGard®

(Chlorhexidine Gluconate
Oral Rinse USP, 0.12%)

ALCOHOL FREE

Rx Only

KEEP OUT OF REACH OF CHILDREN
For questions or comments contact
your dentist or pharmacist.